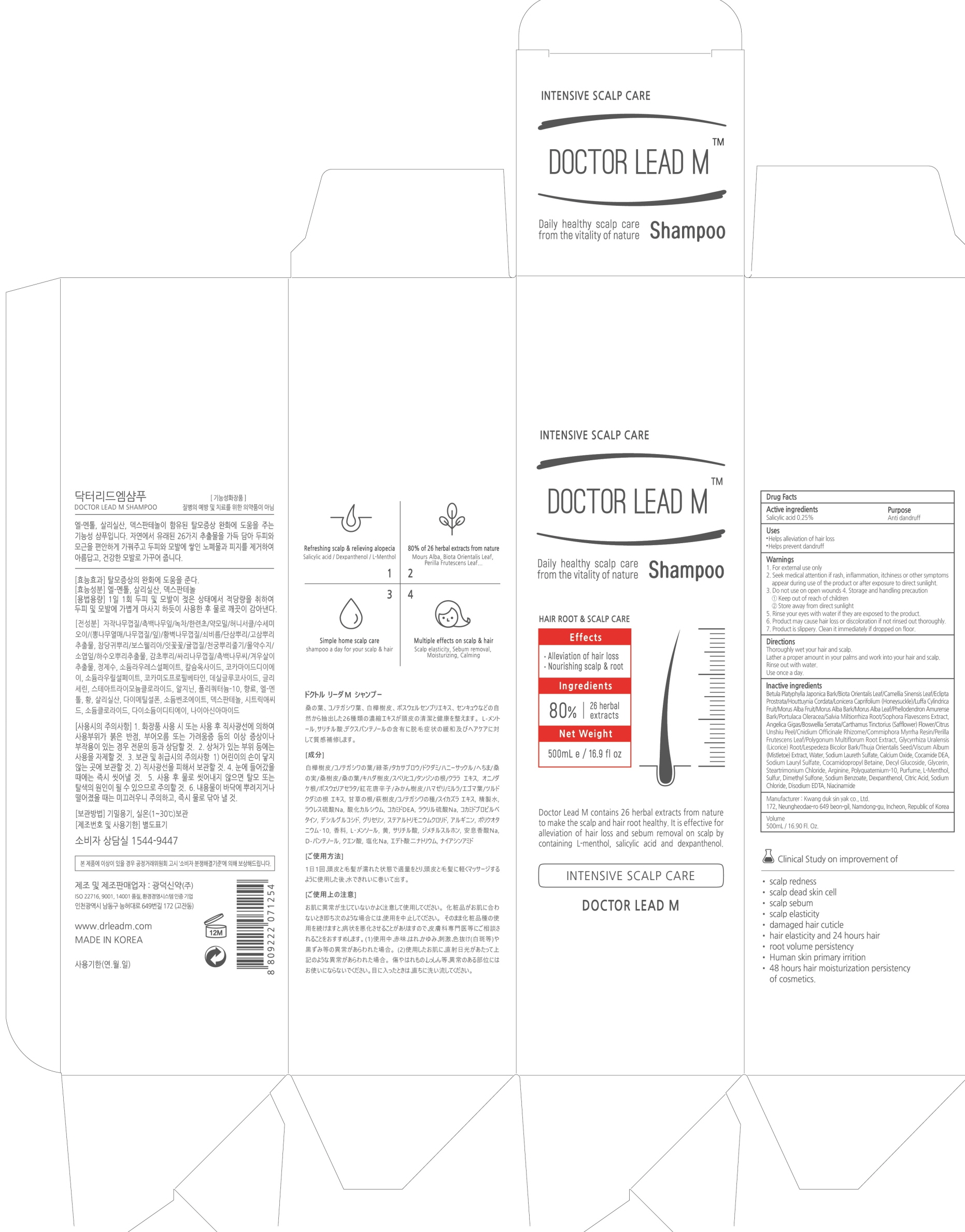 DRUG LABEL: DOCTOR LEAD M
NDC: 71838-0005 | Form: SHAMPOO
Manufacturer: Kwang Duk Sin Yak Co., Ltd.
Category: otc | Type: HUMAN OTC DRUG LABEL
Date: 20190220

ACTIVE INGREDIENTS: Salicylic acid 1.25 g/500 mL
INACTIVE INGREDIENTS: BETULA PLATYPHYLLA BARK; PLATYCLADUS ORIENTALIS LEAF

ACTIVE INGREDIENT

Active ingredient: Salicylic acid 0.25%

INACTIVE INGREDIENT

Inactive ingredients:
Betula Platyphylla Japonica Bark/Biota Orientalis Leaf/Camellia Sinensis Leaf/Eclipta Prostrata/Houttuynia Cordata/Lonicera Caprifolium (Honeysuckle)/Luffa Cylindrica Fruit/Morus Alba Fruit/Morus Alba Bark/Morus Alba Leaf/Phellodendron Amurense Bark/Portulaca Oleracea/Salvia Miltiorrhiza Root/Sophora Flavescens Extract, Angelica Gigas/Boswellia Serrata/Carthamus Tinctorius (Safflower) Flower/Citrus Unshiu Peel/Cnidium Officinale Rhizome/Commiphora Myrrha Resin/Perilla Frutescens Leaf/Polygonum Multiflorum Root Extract, Glycyrrhiza Uralensis (Licorice) Root/Lespedeza Bicolor Bark/Thuja Orientalis Seed/Viscum Album (Mistletoe) Extract, Water, Sodium Laureth Sulfate, Calcium Oxide, Cocamide DEA, Sodium Lauryl Sulfate, Cocamidopropyl Betaine, Decyl Glucoside, Glycerin, Steartrimonium Chloride, Arginine, Polyquaternium-10, Purfume, L-Menthol, Sulfur, Dimethyl Sulfone, Sodium Benzoate, Dexpanthenol, Citric Acid, Sodium Chloride, Disodium EDTA, Niacinamide

PURPOSE

Purpose: Anti dandruff

WARNINGS

1. For external use only
2. Seek medical attention if rash, inflammation, itchiness or other symptoms appear during use of the product or after exposure to direct sunlight.
3. Do not use on open wounds
4. Storage and handling precaution
1) Keep out of reach of children
2) Store away from direct sunlight
5. Rinse your eyes with water if they are exposed to the product.
6. Product may cause hair loss or discoloration if not rinsed out thoroughly.
7. Product is slippery. Clean it immediately if dropped on floor.

KEEP OUT OF REACH OF CHILDREN

Uses

Helps alleviation of hair loss
Helps prevent dandruff

Directions

Thoroughly wet your hair and scalp.
Lather a proper amount in your palms and work into your hair and scalp.
Rinse out with water.
Use once a day.